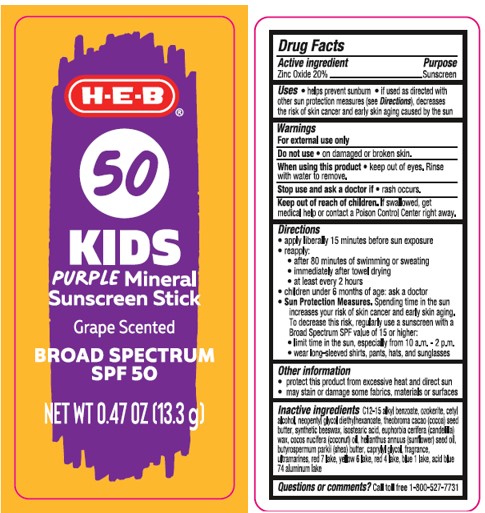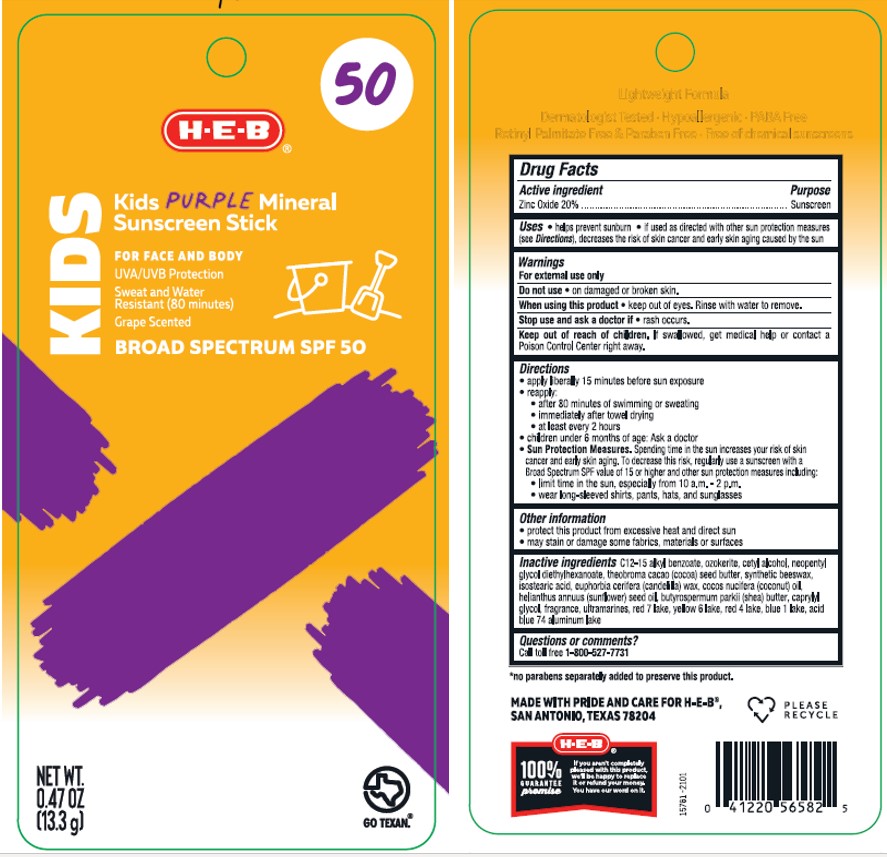 DRUG LABEL: HEB SPF 50 Kids Purple Mineral Sunscreen Stick Grape Scented
NDC: 37808-039 | Form: STICK
Manufacturer: H.E.B.
Category: otc | Type: HUMAN OTC DRUG LABEL
Date: 20241015

ACTIVE INGREDIENTS: ZINC OXIDE 200 mg/1 g
INACTIVE INGREDIENTS: CANDELILLA WAX; SUNFLOWER OIL; SHEA BUTTER; SYNTHETIC BEESWAX; NEOPENTYL GLYCOL DIETHYLHEXANOATE; ISOSTEARIC ACID; CETYL ALCOHOL; COCOA BUTTER; CERESIN; ALKYL (C12-15) BENZOATE; KAOLIN; CAPRYLYL GLYCOL; COCONUT OIL; ULTRAMARINE BLUE; FD&C RED NO. 40; FD&C BLUE NO. 1 ALUMINUM LAKE; D&C RED NO. 7; ROSIN; INDIGOTINDISULFONATE SODIUM; CALCIUM SULFATE ANHYDROUS; FD&C YELLOW NO. 6

HEB SPF 50 Kids Purple Mineral Sunscreen Stick Grape Scented

Active Ingredients

Zinc Oxide 20.0%

Purpose

Sunscreen

Uses

- helps prevent sunburn
- if used as directed with other sun protection measures (see Directions), decreases the risk of skin cancer and early skin aging caused by the sun

Warnings

For external use only

Do not use

• on damaged or broken skin.

When using this product

• keep out of eyes. Rinse with water to remove.

Stop use and ask a doctor if

• rash occurs.

Keep out of reach of children.

If swallowed, get medical help or contact a Poison Control Center right away.

Directions

- apply liberally 15 minutes before sun exposure
- reapply:

• after 80 minutes of swimming or sweating

• immediately after towel drying

• at least every 2 hours

- children under 6 months of age: Ask a doctor
- Sun Protection Measures. Spending time in the sun increases your risk of skin cancer and early skin aging. To decrease this risk, regularly use a sunscreen with a Broad Spectrum SPF value of 15 or higher and other sun protection measures including:

• limit time in the sun, especially from 10 a.m. - 2 p.m.

• wear long-sleeved shirts, pants, hats, and sunglasses

Other Information

- protect the product in this container from excessive heat and direct sun
- may stain or damage some fabrics, materials or surfaces

Inactive Ingredient(s)

C12-15 alkyl benzoate, ozokerite, cetyl alcohol, neopentyl glycol diethylhexanoate, theobroma cacao (cocoa) seed butter, synthetic beeswax, isostearic acid, euphorbia cerifera (candelilla) wax, cocos nucifera (coconut) oil, helianthus annuus (sunflower) seed oil, butyrospermum parkii (shea) butter, caprylyl glycol, fragrance, ultramarines, red 7 lake, yellow 6 lake, red 4 lake, blue 1 lake, acid blue 74 aluminum lake